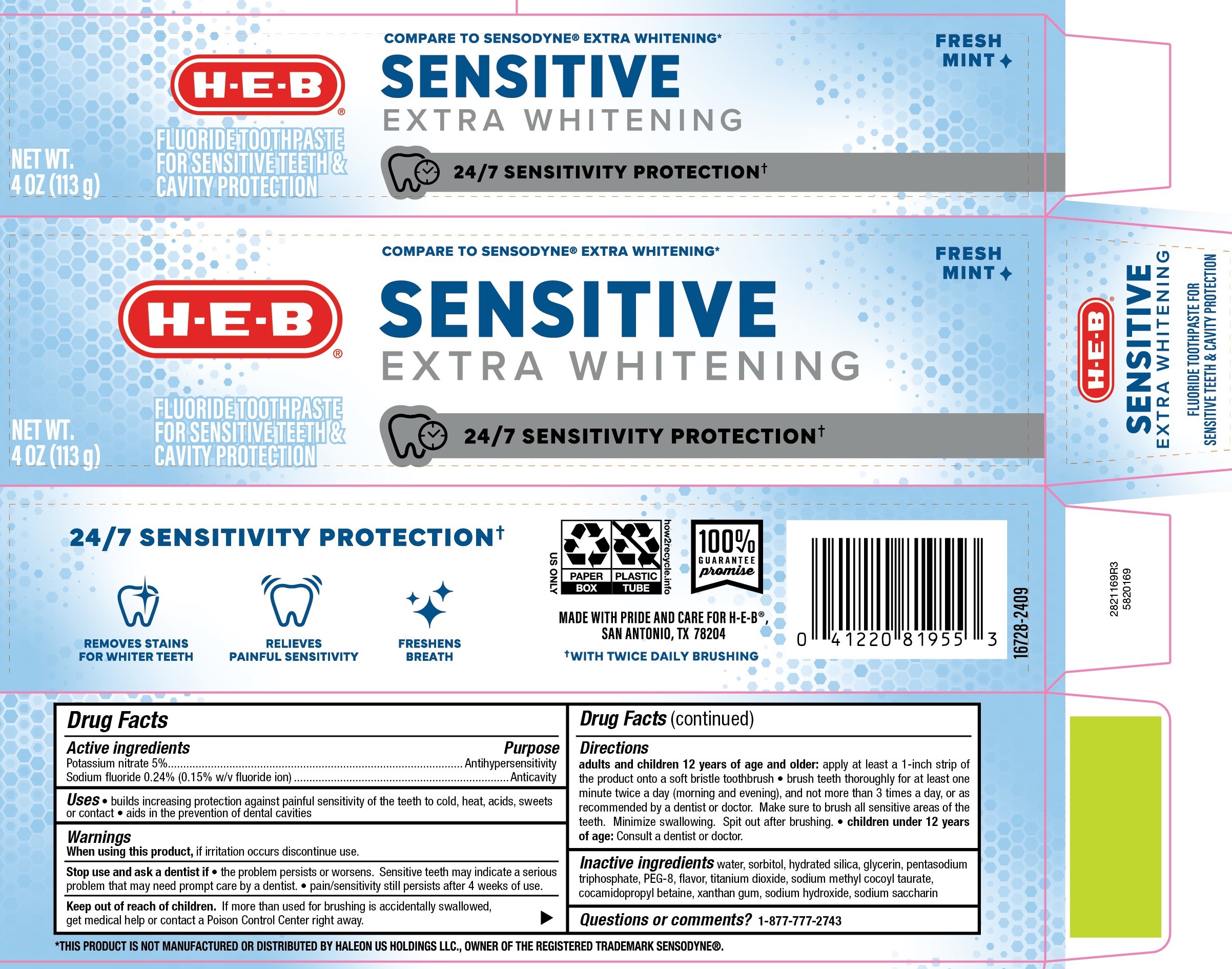 DRUG LABEL: HEB
NDC: 37808-961 | Form: PASTE, DENTIFRICE
Manufacturer: HEB
Category: otc | Type: HUMAN OTC DRUG LABEL
Date: 20250808

ACTIVE INGREDIENTS: SODIUM FLUORIDE 0.15 g/100 g; POTASSIUM NITRATE 5 g/100 g
INACTIVE INGREDIENTS: WATER; SACCHARIN SODIUM; SODIUM TRIPOLYPHOSPHATE; POLYETHYLENE GLYCOL 400; SORBITOL; TITANIUM DIOXIDE; SODIUM HYDROXIDE; GLYCERIN; XANTHAN GUM; HYDRATED SILICA; COCAMIDOPROPYL BETAINE; SODIUM METHYL COCOYL TAURATE

5820169 HEB Sensitive Extra Whitening Toothpaste

Drug Facts

Active ingredients

Potassium nitrate 5%

Sodium fluoride 0.24% (0.15% w/v fluoride ion)

Purpose

Antihypersensitivity

Anticavity

Uses

- builds increasing protection against painful sensitivity of the teeth to cold, heat, acids, sweets or contact
- aids in the prevention of dental cavities

Warnings

If pain/sensitivity still persists after 4 weeks of use, please visit your dentist.

Stop use and ask a dentist if the problem worsens. Sensitive teeth may indicate a serious problem that may need prompt care by a dentist.

Keep out of reach of children. If more than used for brushing is accidentally swallowed, get medical help or contact a Poison Control Center right away.

Directions

Adults and children 12 years of age and older: Apply at least a 1-inch strip of the product onto a soft bristle toothbrush.

- Brush teeth thoroughly for at least one minute, preferably after each meal or at least twice a day (morning and evening) or as recommended by a dentist or physican. Make sure to brush all sensitive areas of the teeth. Minimize swallowing. Spit out after brushing.
- Children under 12 years of age: Consult a dentist or doctor.

Inactive ingredients

water, sorbitol, hydrated silica, glycerin, pentasodium triphosphate, PEG-8, flavor, titanium dioxide, sodium methyl cocoyl taurate, cocamidopropyl betaine, xanthan gum, sodium hydroxide, sodium saccharin

STORAGE AND HANDLING

Store in a cool dry place. Keep tube capped when not in use.

Questions or Comments? CALL 1-877-777-2748

MADE WITH PRIDE AND CARE FOR H-E-B®

SAN ANTONIO, TX 78204

MADE IN USA